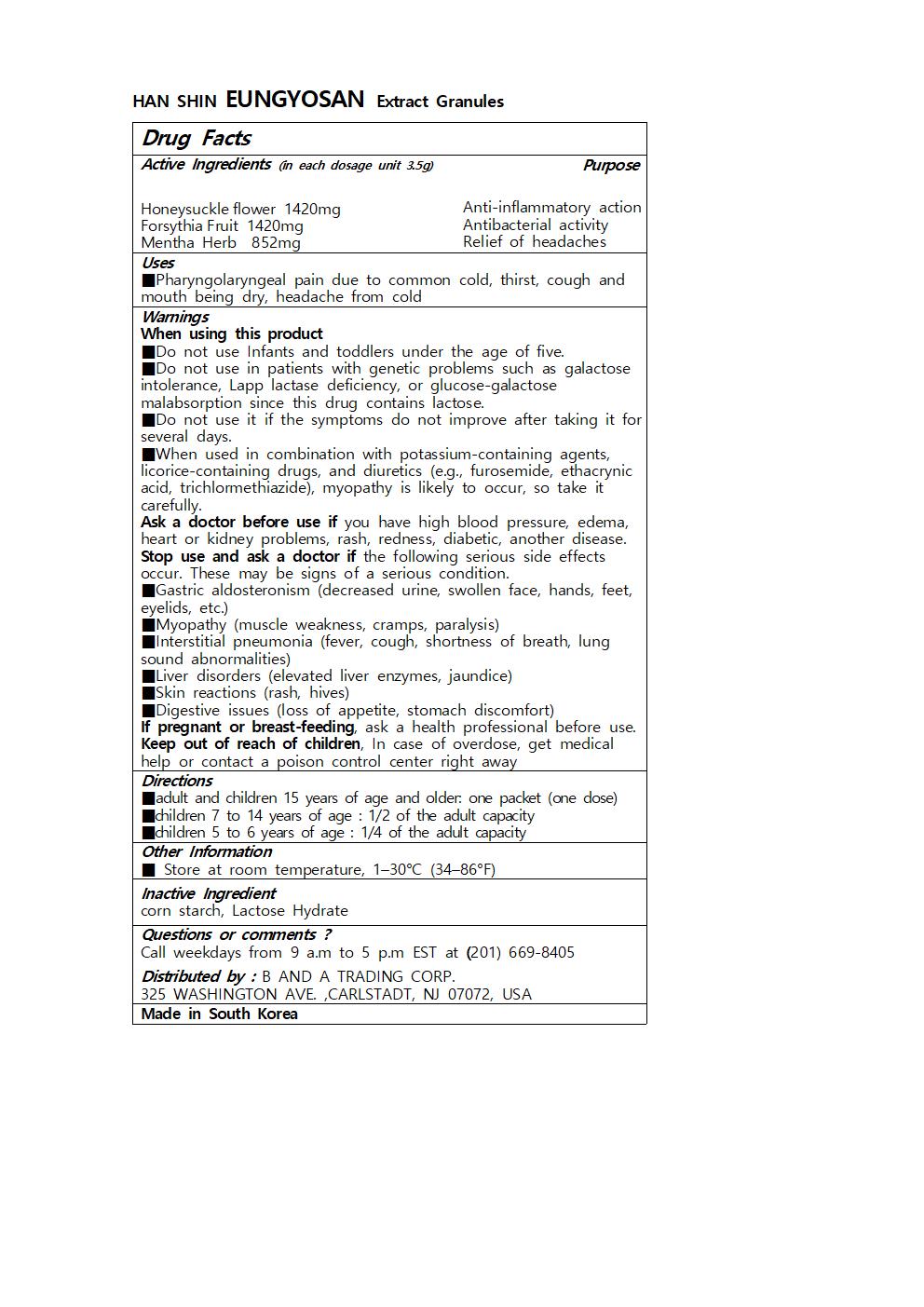 DRUG LABEL: HAN SHIN EUNGYOSAN Extract Granules
NDC: 73466-0031 | Form: GRANULE
Manufacturer: MISOCOS
Category: otc | Type: HUMAN OTC DRUG LABEL
Date: 20250301

ACTIVE INGREDIENTS: FORSYTHIA SUSPENSA FRUIT 1420 mg/3.5 g; LONICERA HYPOGLAUCA FLOWER 1420 mg/3.5 g
INACTIVE INGREDIENTS: LACTOSE MONOHYDRATE; MENTHA ARVENSIS TOP

Drug Facts

ACTIVE INGREDIENT

Honeysuckleflower 1420mg

ForsythiaFruit 1420mg

Mentha Herb 852mg

INACTIVE INGREDIENT

corn starch, Lactose Hydrate

PURPOSE

■Pharyngolaryngeal pain due to common cold, thirst, cough and mouth being dry, headache from cold

keep out of reach of the children

Directions

■adult and children 15 years of age and older: one packet (one dose)

■children 7 to 14 years of age : 1/2 of the adult capacity

■children 5 to 6 years of age : 1/4 of the adult capacity

Warnings

When using this product

■Do not use Infants and toddlers under the age of five.

■Do not use in patients with genetic problems such as galactose intolerance, Lapp lactase deficiency, or glucose-galactose malabsorption since this drug contains lactose.

■Do not use it if the symptoms do not improve after taking it for several days.

■When used in combination with potassium-containing agents, licorice-containing drugs, and diuretics (e.g., furosemide, ethacrynic acid, trichlormethiazide), myopathy is likely to occur, so take it carefully.

Ask a doctor before use if you have high blood pressure, edema, heart or kidney problems, rash, redness, diabetic, another disease.

Stop use and ask a doctor if the following serious side effects occur. These may be signs of a serious condition.

■Gastric aldosteronism (decreased urine, swollen face, hands, feet, eyelids, etc.)

■Myopathy (muscle weakness, cramps, paralysis)

■Interstitial pneumonia (fever, cough, shortness of breath, lung sound abnormalities)

■Liver disorders (elevated liver enzymes, jaundice)

■Skin reactions (rash, hives)

■Digestive issues (loss of appetite, stomach discomfort)

If pregnant or breast-feeding, ask a health professional before use.

Keep out of reach of children, In case of overdose, get medical help or contact a poison control center right away

DOSAGE AND ADMINISTRATION

for oral use only